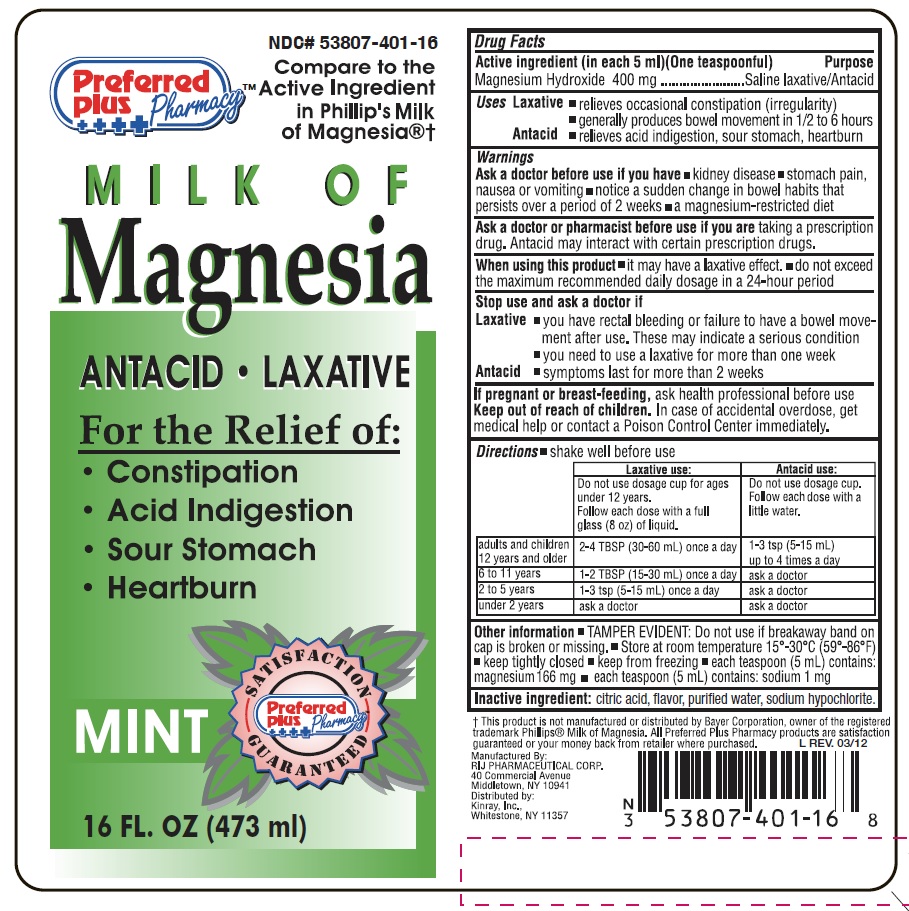 DRUG LABEL: Milk of Magnesia
NDC: 53807-401 | Form: LIQUID
Manufacturer: Rij Pharmaceutical Corporation
Category: otc | Type: HUMAN OTC DRUG LABEL
Date: 20180430

ACTIVE INGREDIENTS: MAGNESIUM HYDROXIDE 400 mg/5 mL
INACTIVE INGREDIENTS: CITRIC ACID MONOHYDRATE; WATER; SODIUM HYPOCHLORITE

Drug Facts

Active Ingredient (in each 5 mL) One teaspoonful)

Magnesium Hydroxide 400 mg

Purpose

Saline laxative/Antacid

Use

Laxative

- relieves occasional constipation (irregularity).
- generally produces bowel movement in ½ to 6 hours.

Antacid

- relieves acid indigestion, sour stomach, heartburn.

Warnings

Ask a doctor before use if you have

- kidney disease
- stomach pain, nausea or vomiting
- notice a sudden change in bowel habits that persists over a period of 2 weeks
- a magnesium-restricted diet

Ask a doctor or pharmacist before use if you are

taking a prescription drug. Antacid may interact with certain prescription drugs.

When using this product

- it may have a laxative effect
- do not exceed the maximum recommended daily dosgae in a 24-hour period

Stop use and ask a doctor if

Laxative

- you have rectal bleeding or failure to have a bowel movement after use. These may indicate a serious condition.
- you need to use a laxative for more than one week

Antacid

- symptoms last for more than 2 weeks.

If pregnant or breast-feeding,

ask a health professional before use.

Keep out of reach of children.

In case of accidental overdose, get medical help or contact a Poison Control Center immediately.

Directions

- shake well before use

 | Laxative use: | Antacid use
 | Do not use dosage cup for ages under 12 years.; Follow each dose with a full glass (8 oz) of liquid. | Do not use dosage cup.; Follow each dose with a little water.
adults and children 12 years and older | 2-4 TBSP (30-60 mL) once a day | 1-3 tsp (5-15 mL) up to 4 times a day
6 to 11 years | 1-2 TBSP (15-30 mL) once a day | ask a doctor
2 to 5 years | 1-3 tsp (5-15 mL) once a day | ask a doctor
under 2 years | ask a doctor | ask a doctor

Other information

- TAMPER EVIDENT: Do not use if breakaway band on cap is broken or missing.
- Store at room temperature 15º - 30ºC (59º - 86ºF)
- keep tightly closed
- keep from freezing
- each teaspoon (5 mL) contains: magnesium 166 mg
- each teaspoon (5 mL) contains: sodium 1 mg

Inactive ingredients

citric acid, flavor, purified water, sodium hypochlorite.